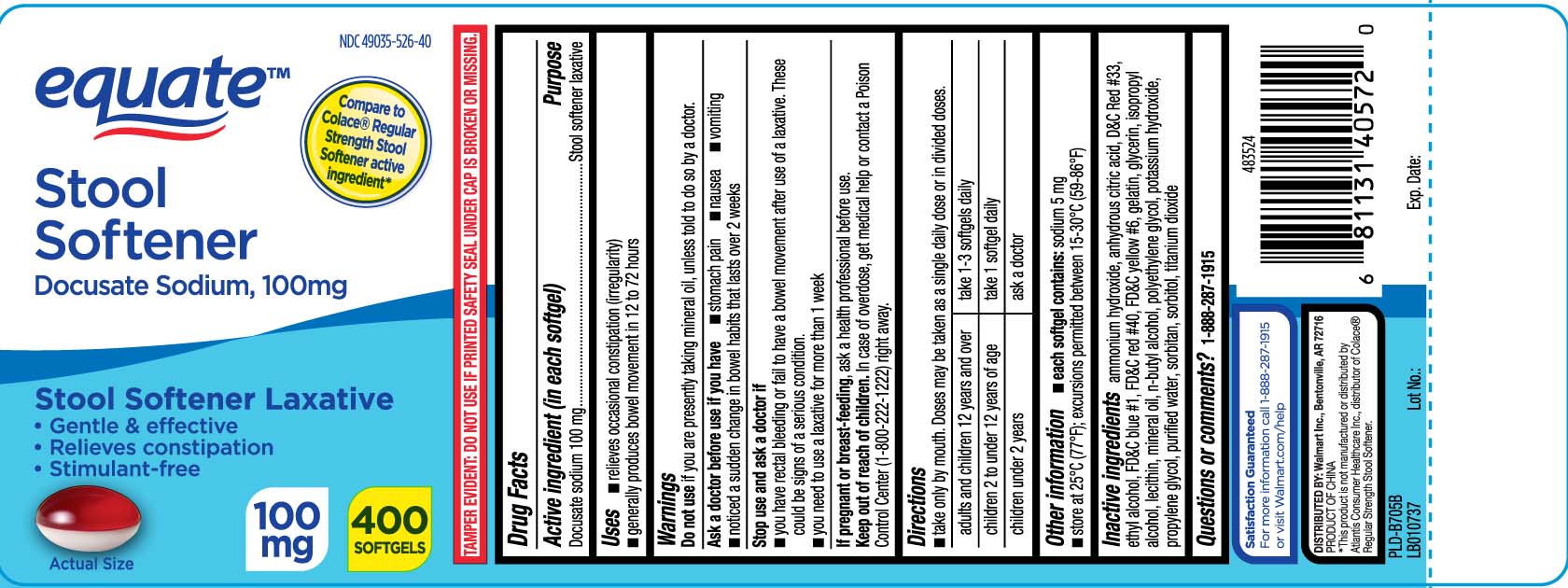 DRUG LABEL: Stool Softener Laxative
NDC: 49035-526 | Form: CAPSULE, LIQUID FILLED
Manufacturer: EQUATE (Wal-Mart Stores, Inc.) (see also WAL-MART INC)
Category: otc | Type: HUMAN OTC DRUG LABEL
Date: 20260203

ACTIVE INGREDIENTS: DOCUSATE SODIUM 100 mg/1 1
INACTIVE INGREDIENTS: D&C RED NO. 33; FD&C BLUE NO. 1; FD&C RED NO. 40; FD&C YELLOW NO. 6; GELATIN; GLYCERIN; POLYETHYLENE GLYCOL, UNSPECIFIED; PROPYLENE GLYCOL; WATER; SORBITAN; SORBITOL; TITANIUM DIOXIDE; AMMONIA; ISOPROPYL ALCOHOL; LECITHIN, SOYBEAN; MINERAL OIL; BUTYL ALCOHOL; ALCOHOL; POTASSIUM HYDROXIDE

Drug Facts

Active ingredient (in each softgel)

Docusate sodium 100 mg

Purpose

Stool softener laxative

Uses

- relieves occasional constipation (irregularity)
- generally produces bowel movement in 12 to 72 hours

Warnings

Do not use

if you are presently taking mineral oil, unless told to do so by a doctor.

Ask a doctor before use if you have

- stomach pain
- nausea
- vomiting
- a sudden change in bowel habits that lasts over 2 weeks

Stop use and ask a doctor if

- you have rectal bleeding or fail to have a bowel movement after use of a laxative. These could be signs of a serious condition.
- you need to use a laxative for more than 1 week

If pregnant or breast-feeding,

ask a health professional before use.

Keep out of reach of children.

In case of overdose, get medical help or contact a Poison Control Center (1-800-222-1222) right away.

Directions

- take only by mouth. Doses may be taken as a single daily dose or in divided doses.

adults and children 12 years and over | take 1-3 softgels daily
children 2 to under 12 years of age | take 1 softgel daily
children under 2 years | ask a doctor

Other information

- each softgel contains:sodium 5 mg
- store at 25ºC (77ºF); excursions permitted between 15-30ºC (59-86ºF)

Inactive ingredients

ammonium hydroxide, anhydrous citric, D&C red #33, ethyl alcohol, FD&C blue #1* FD&C red #40, FD&C yellow #6, gelatin, glycerin, isopropyl alcohol, lecithin, mineral oil, n-butyl alcohol, polyethylene glycol, potassium hydroxide, propylene glycol, purified water, sorbitan, sorbitol, titanium dioxide

Questions or comments?

Call 1--888-287-1915

Principal Display Panel

Compare to Colace® Regular Strength Stool Softener active ingredient*

Stool Softener

Docusate Sodium, 100 mg

Stool Softener Laxative

- Gentle & effective
- Relieves constipation
- Stimulant-free

SOFTGELS

*This product is not manufactured or distributed by Atlantis Consumer Healthcare Inc., distributor of Colace® Regular Strength Stool Softener.

TAMPER EVIDENT: DO NOT USE IF PRINTED SAFETY SEAL UNDER CAP IS BROKEN OR MISSING.

DISTRIBUTED BY: Walmart Inc.,

Bentonville, AR 72716

Product Label

EQUATE Stool Softener Laxative